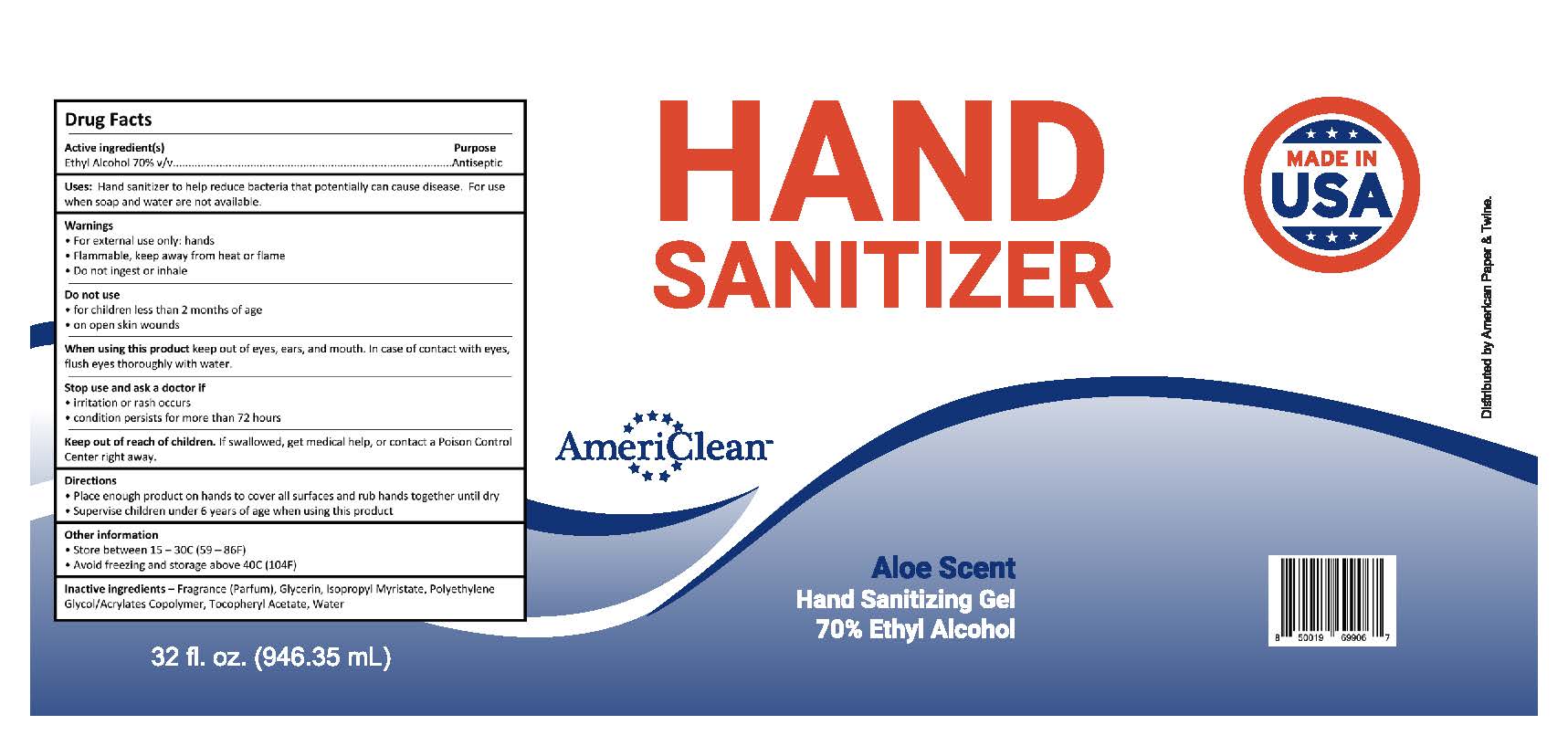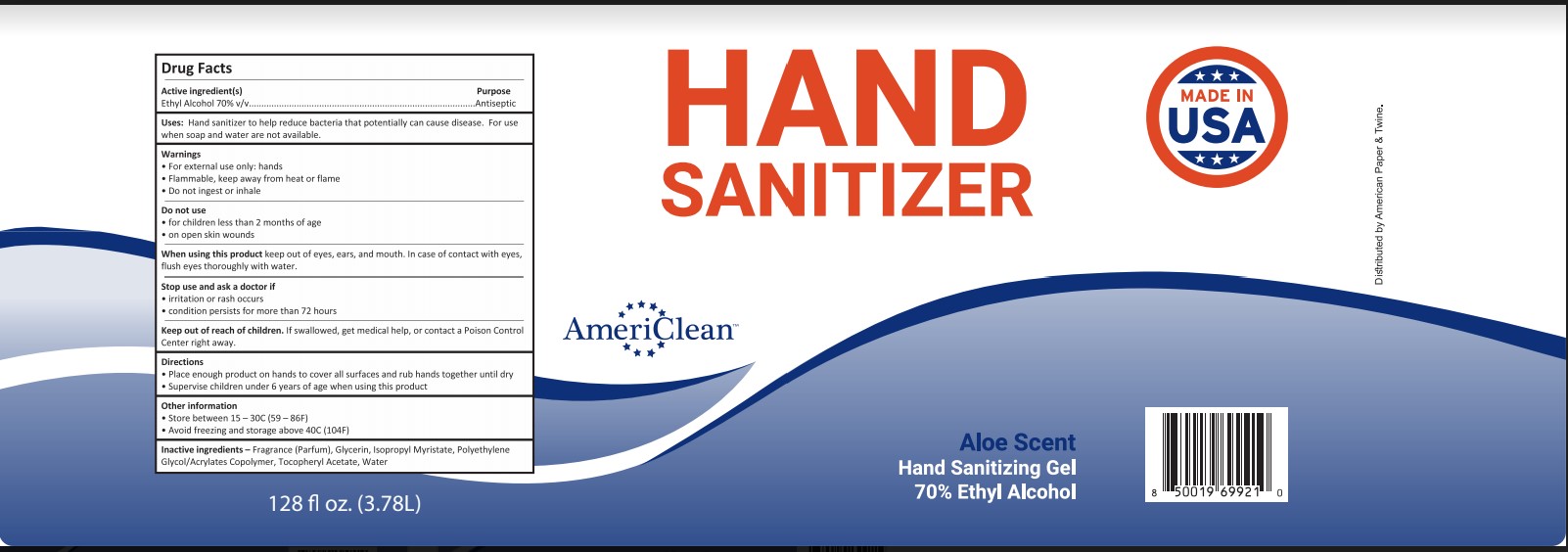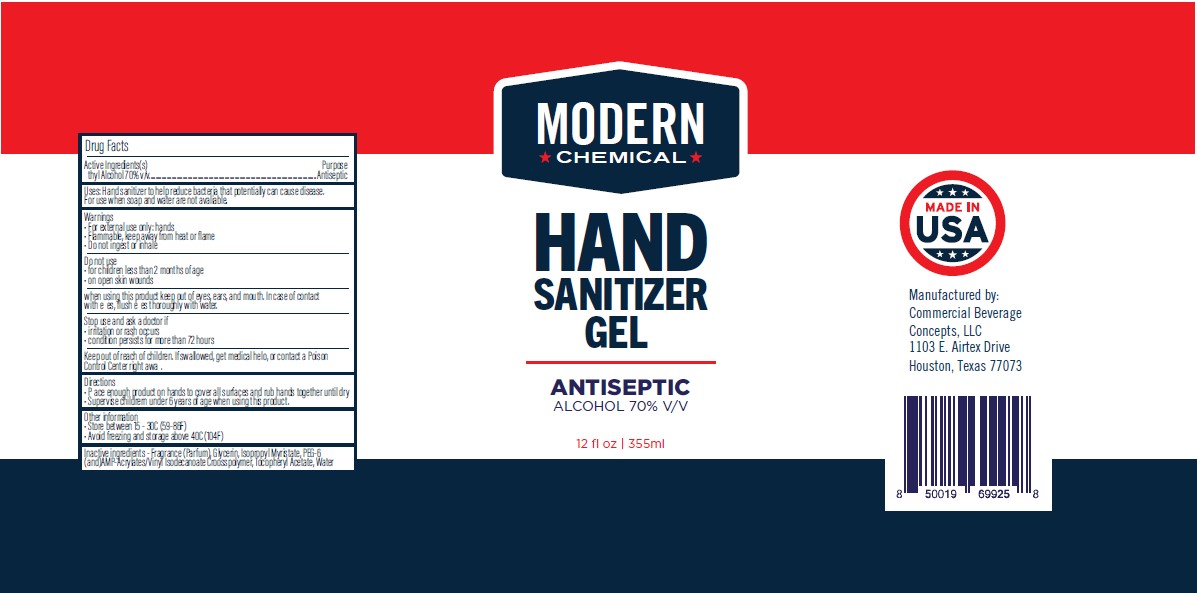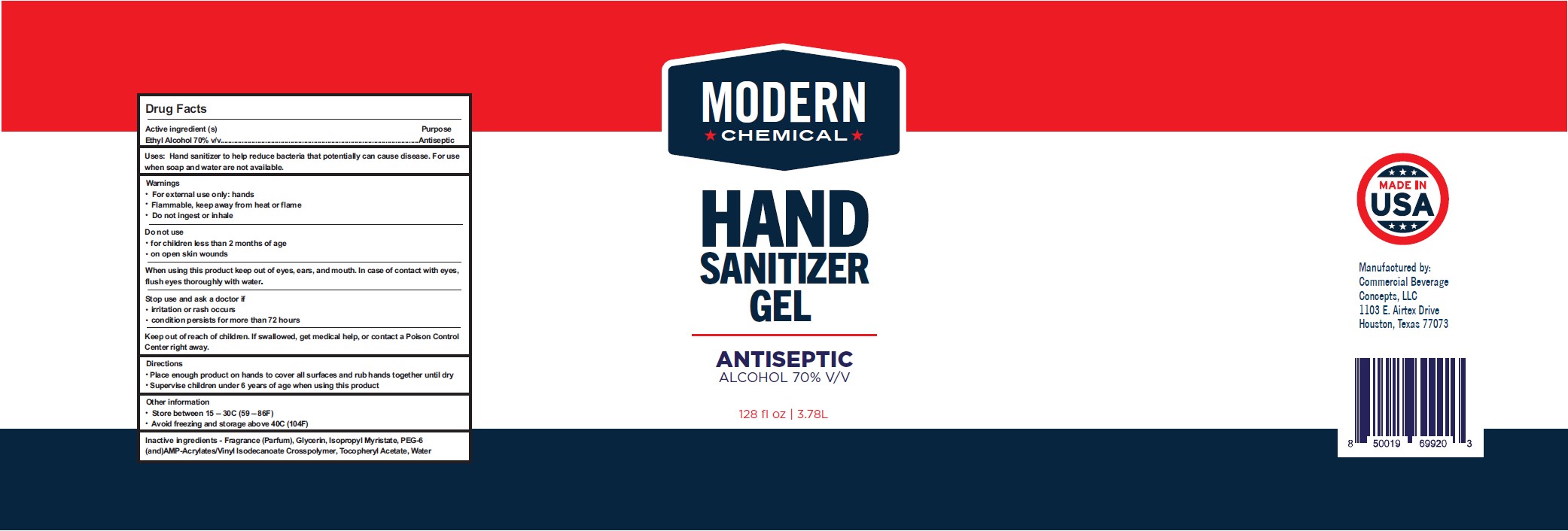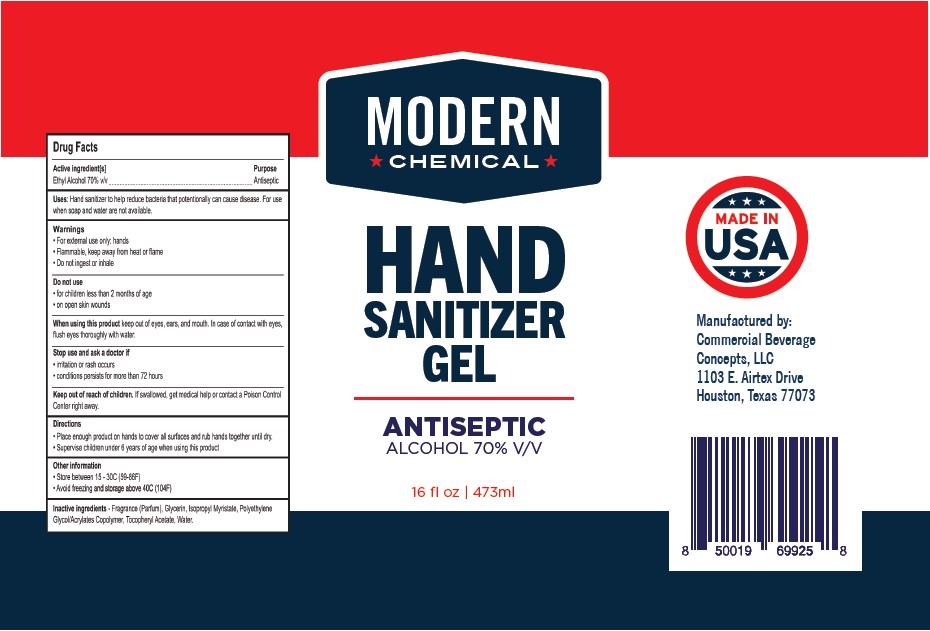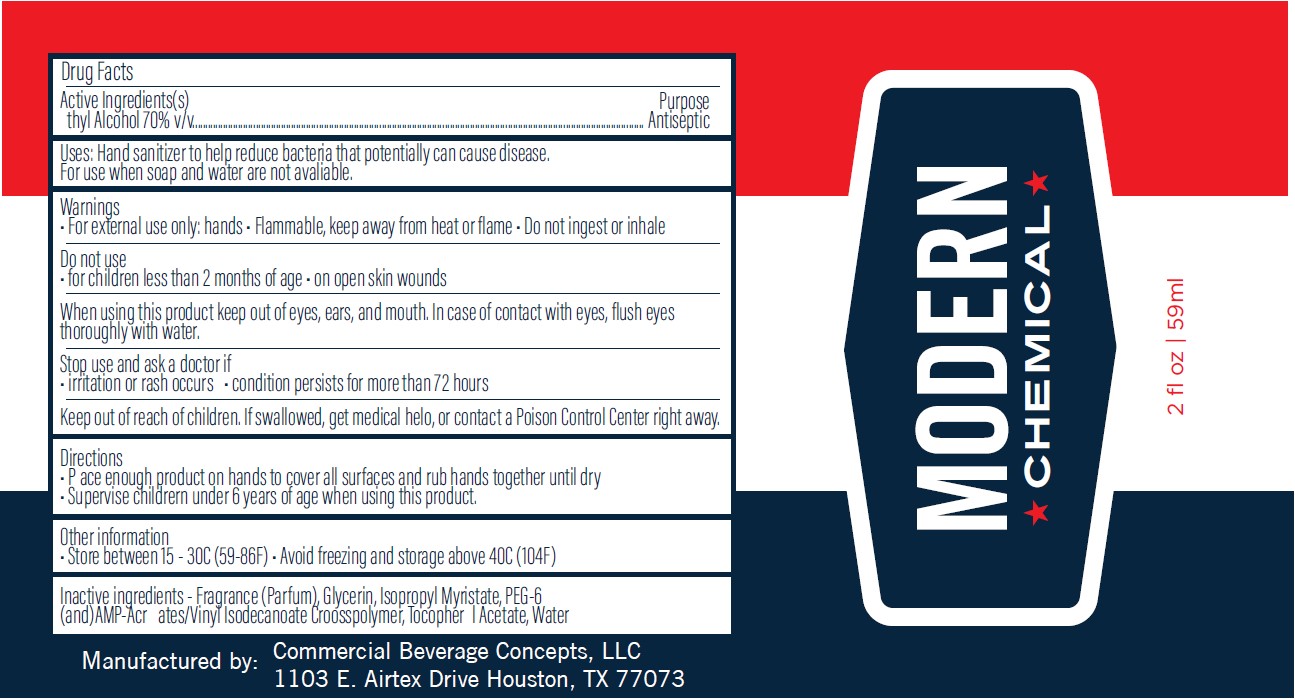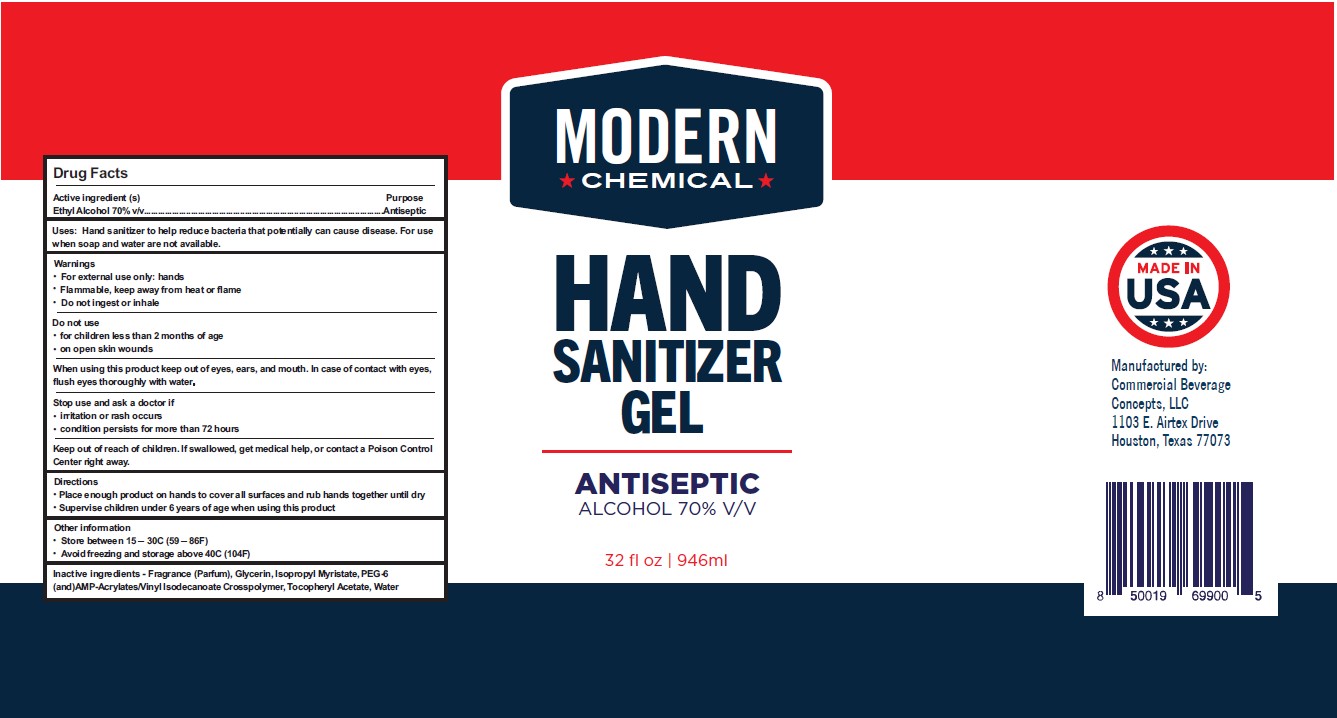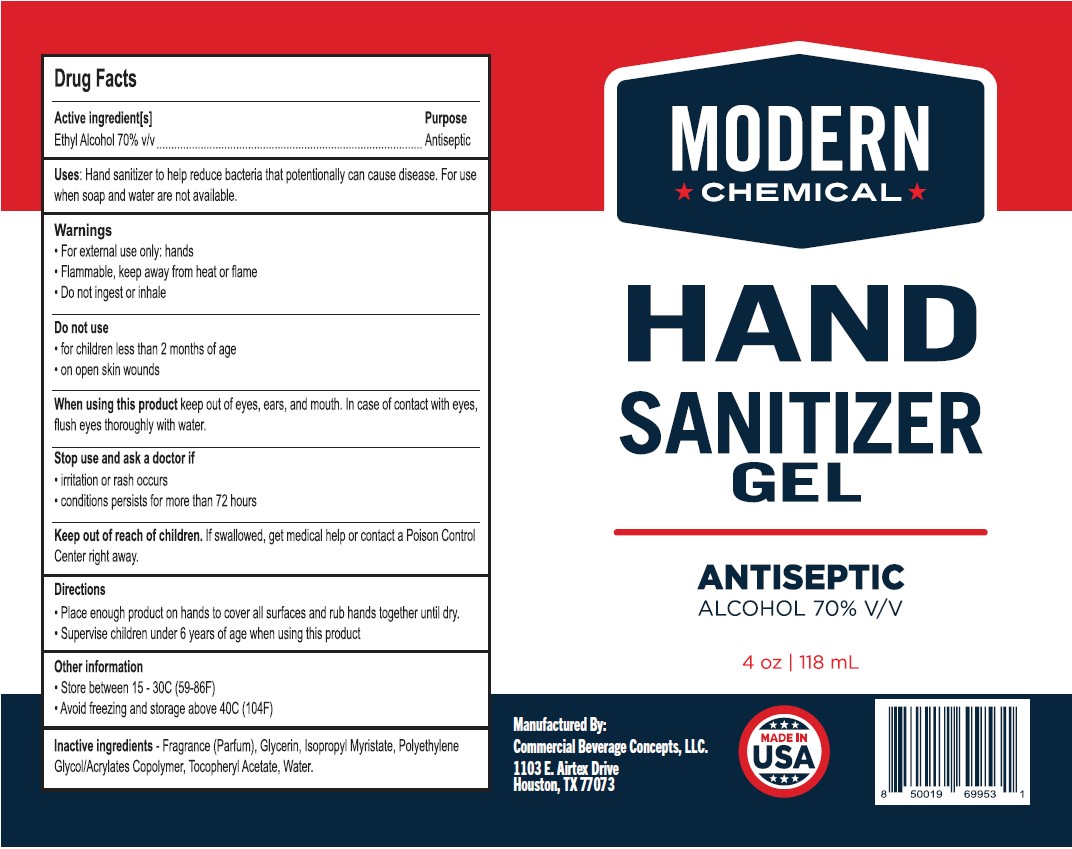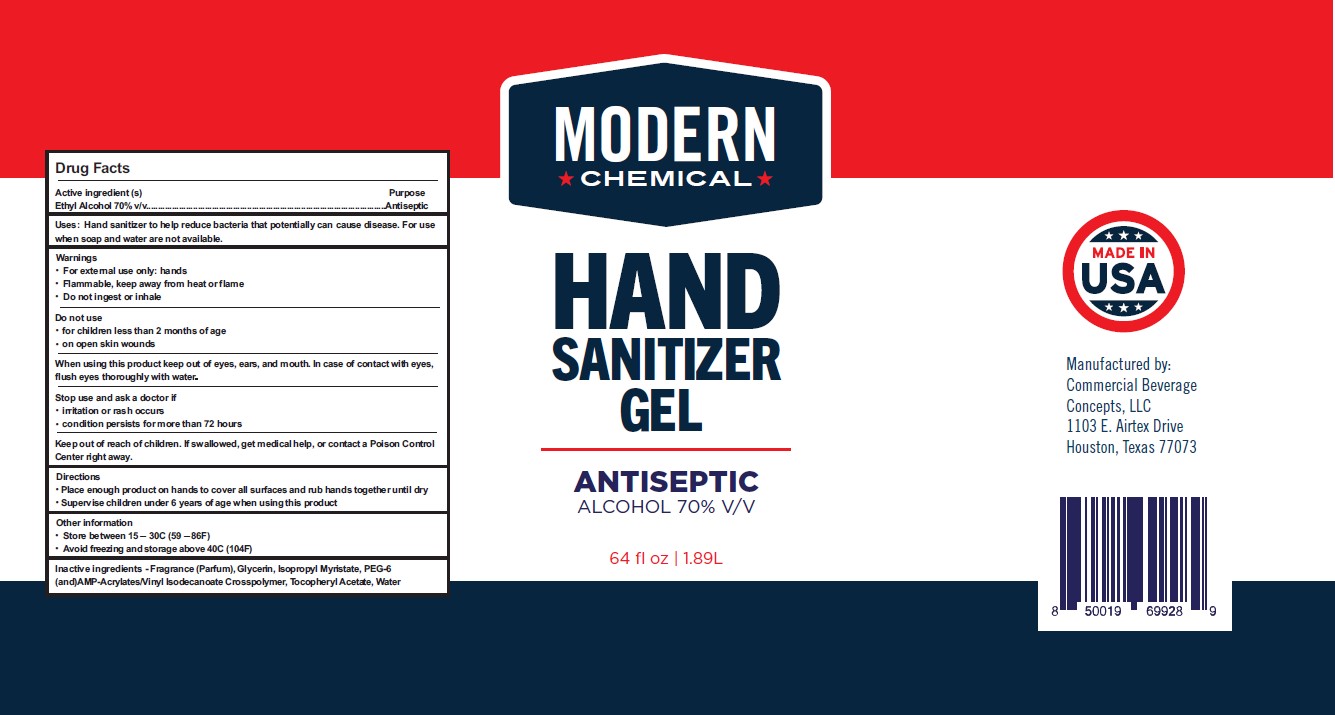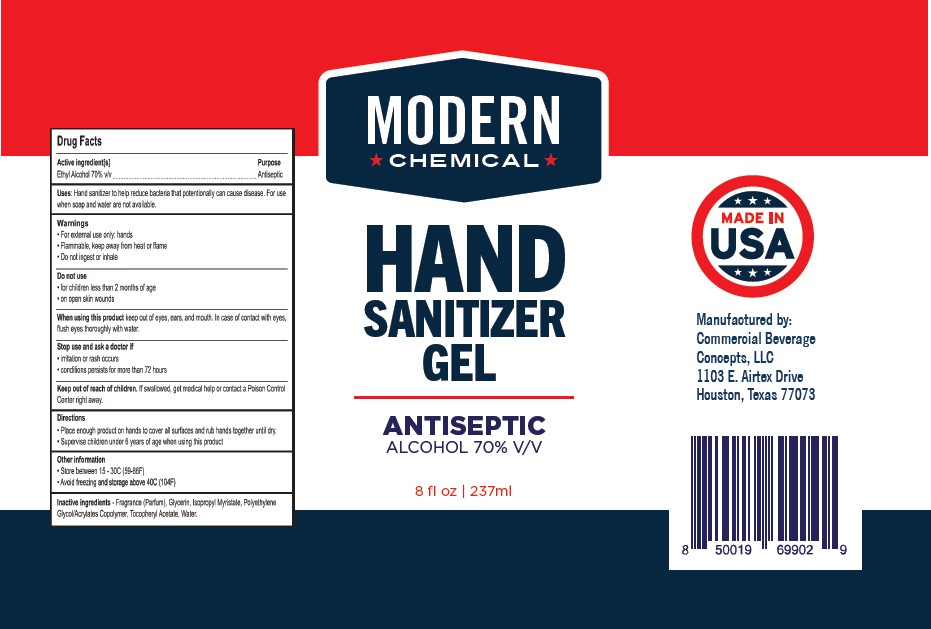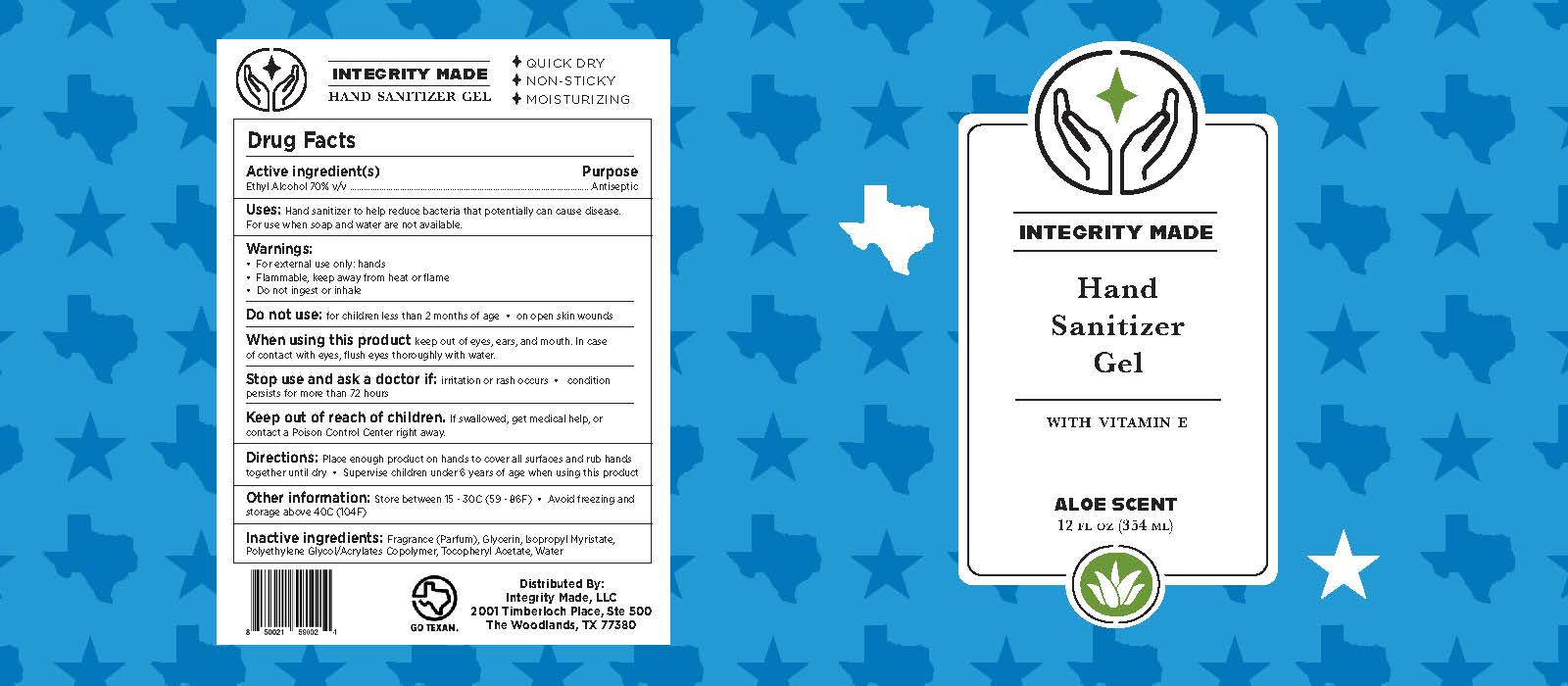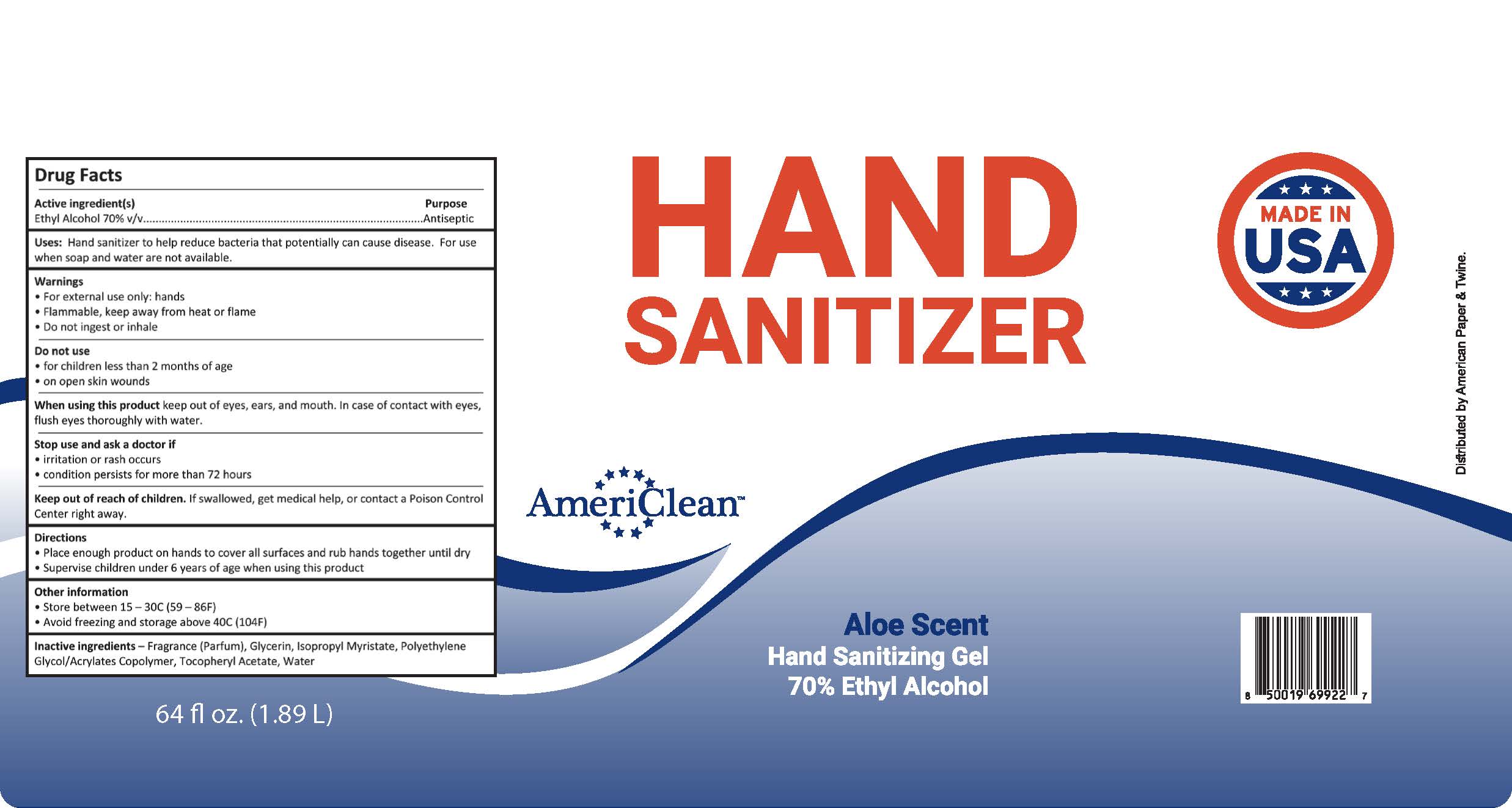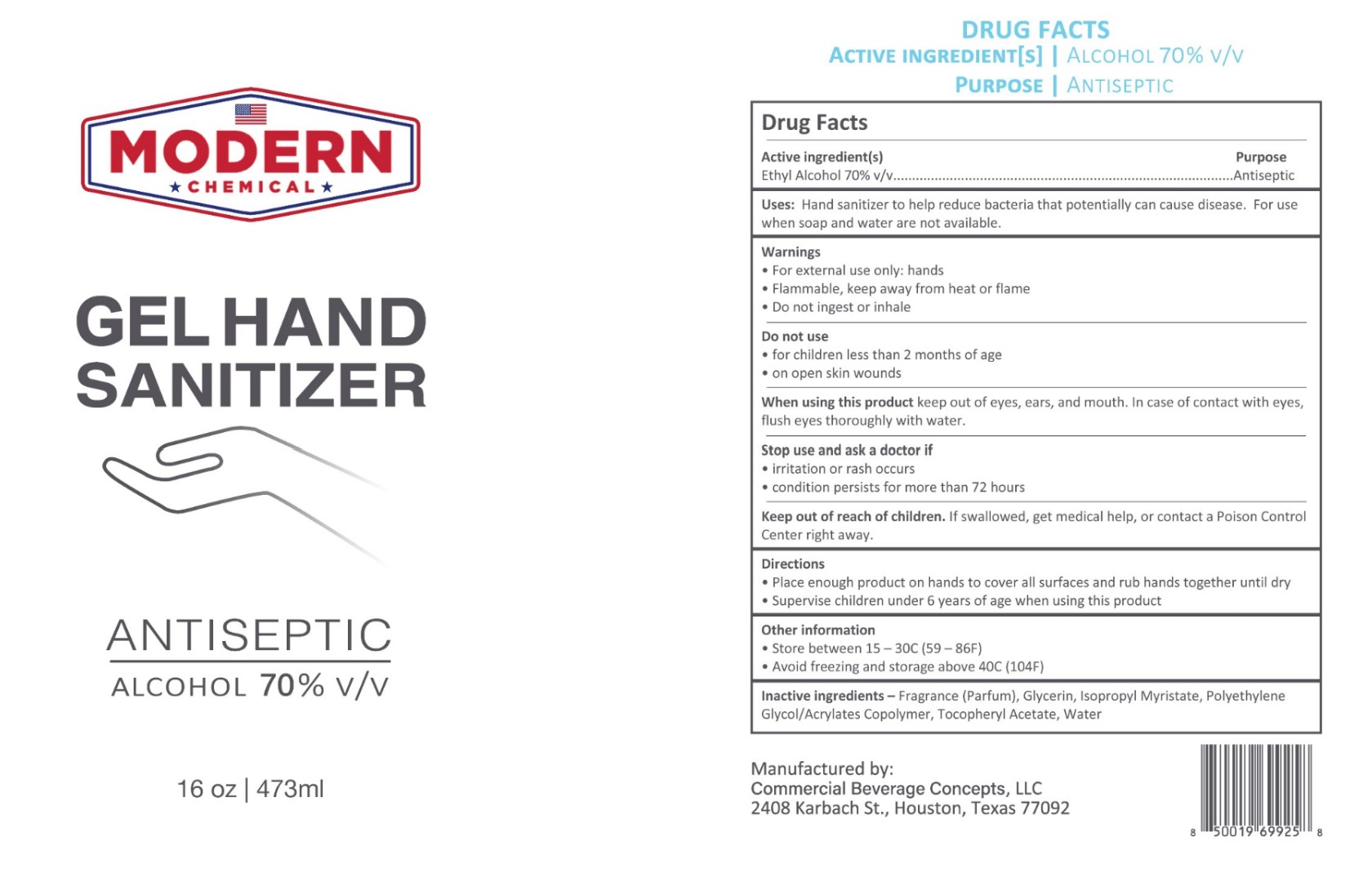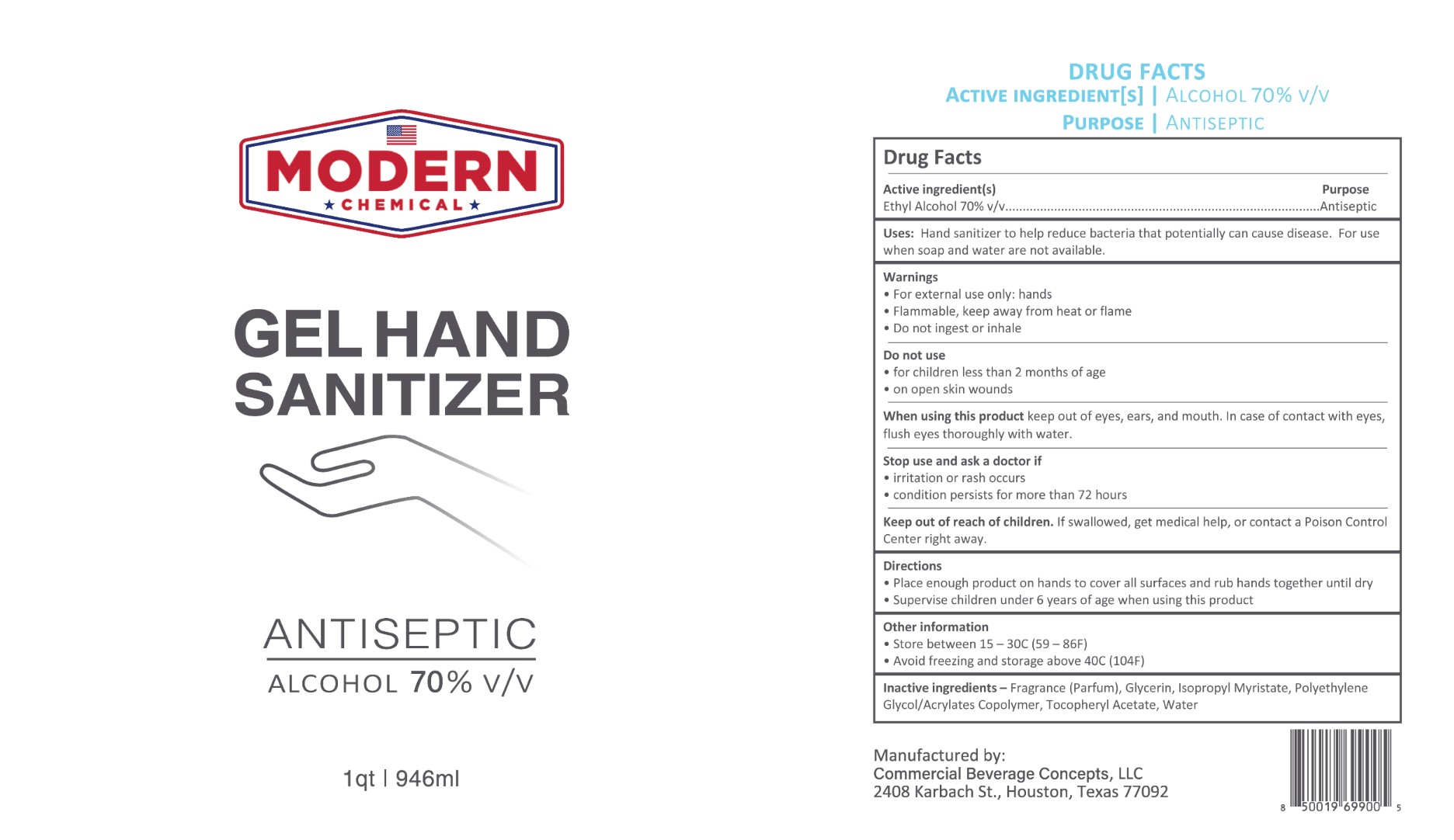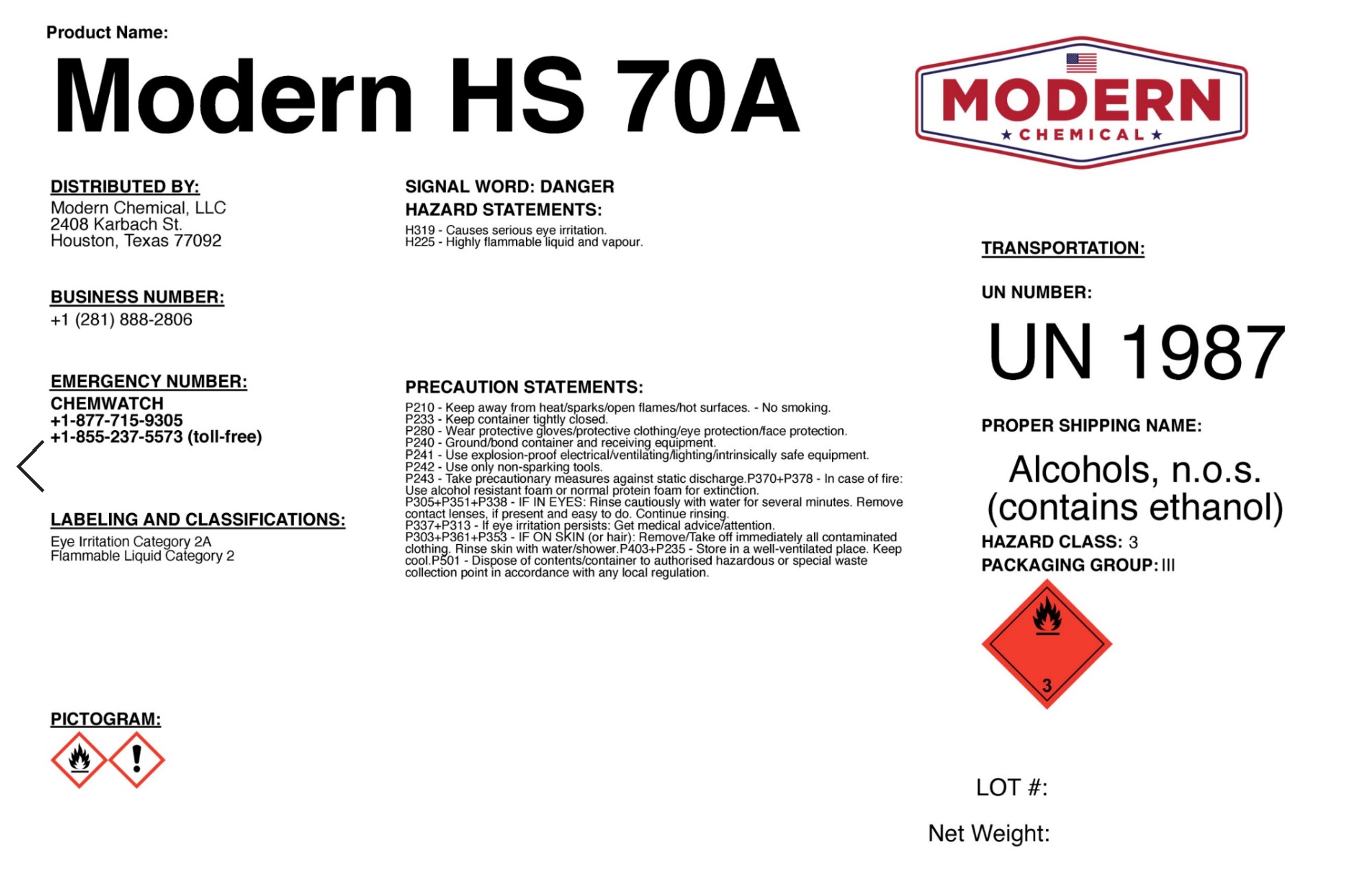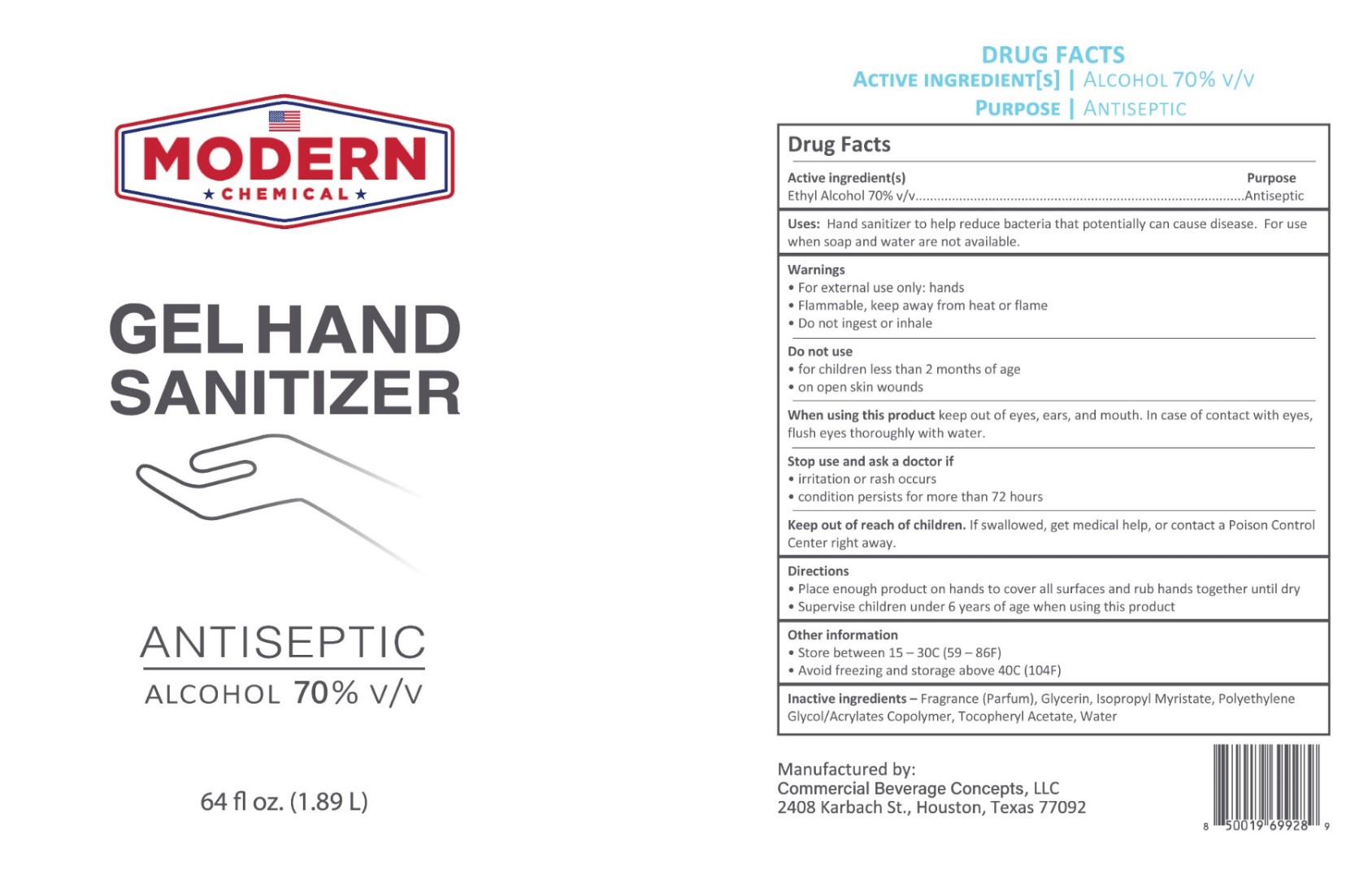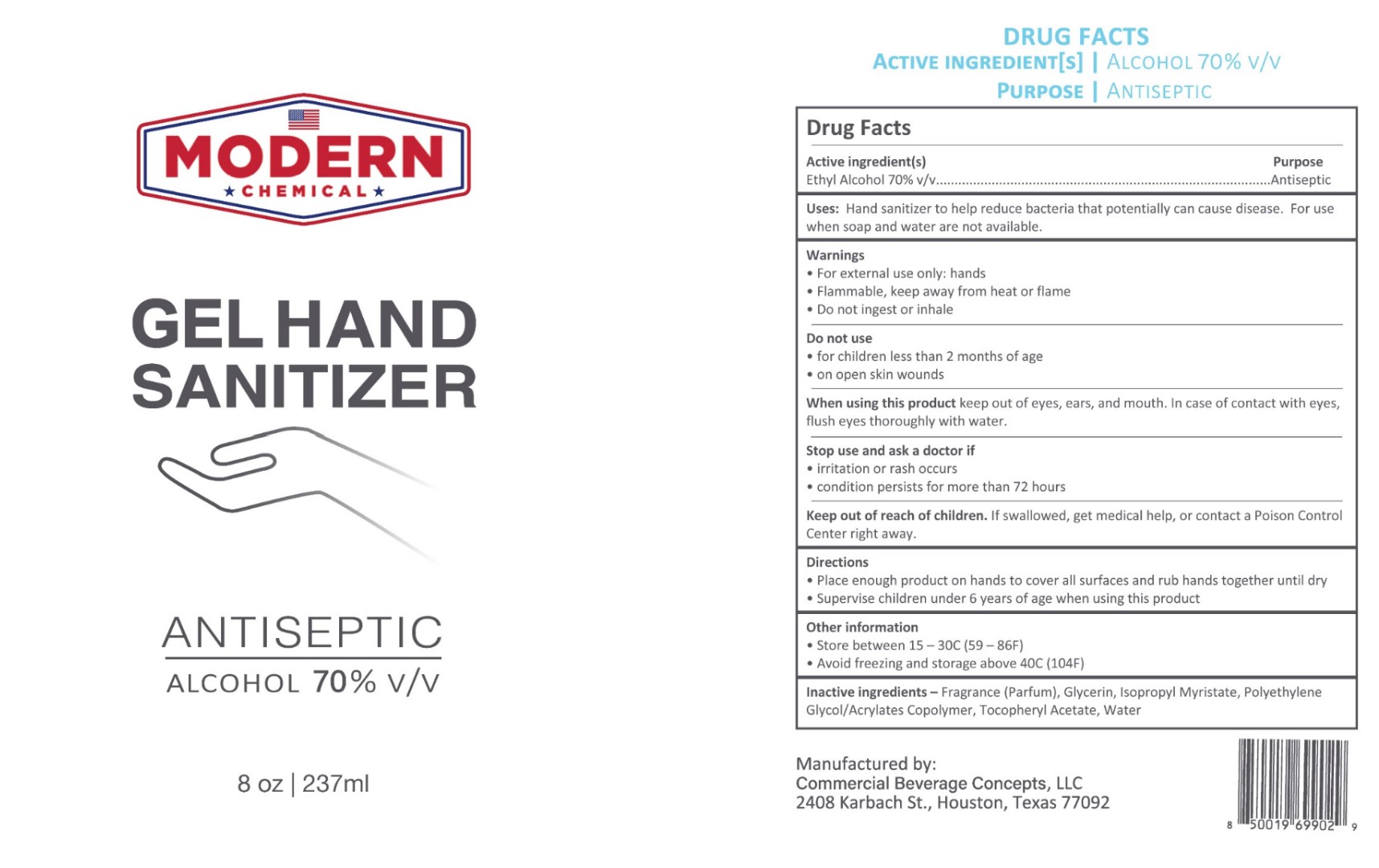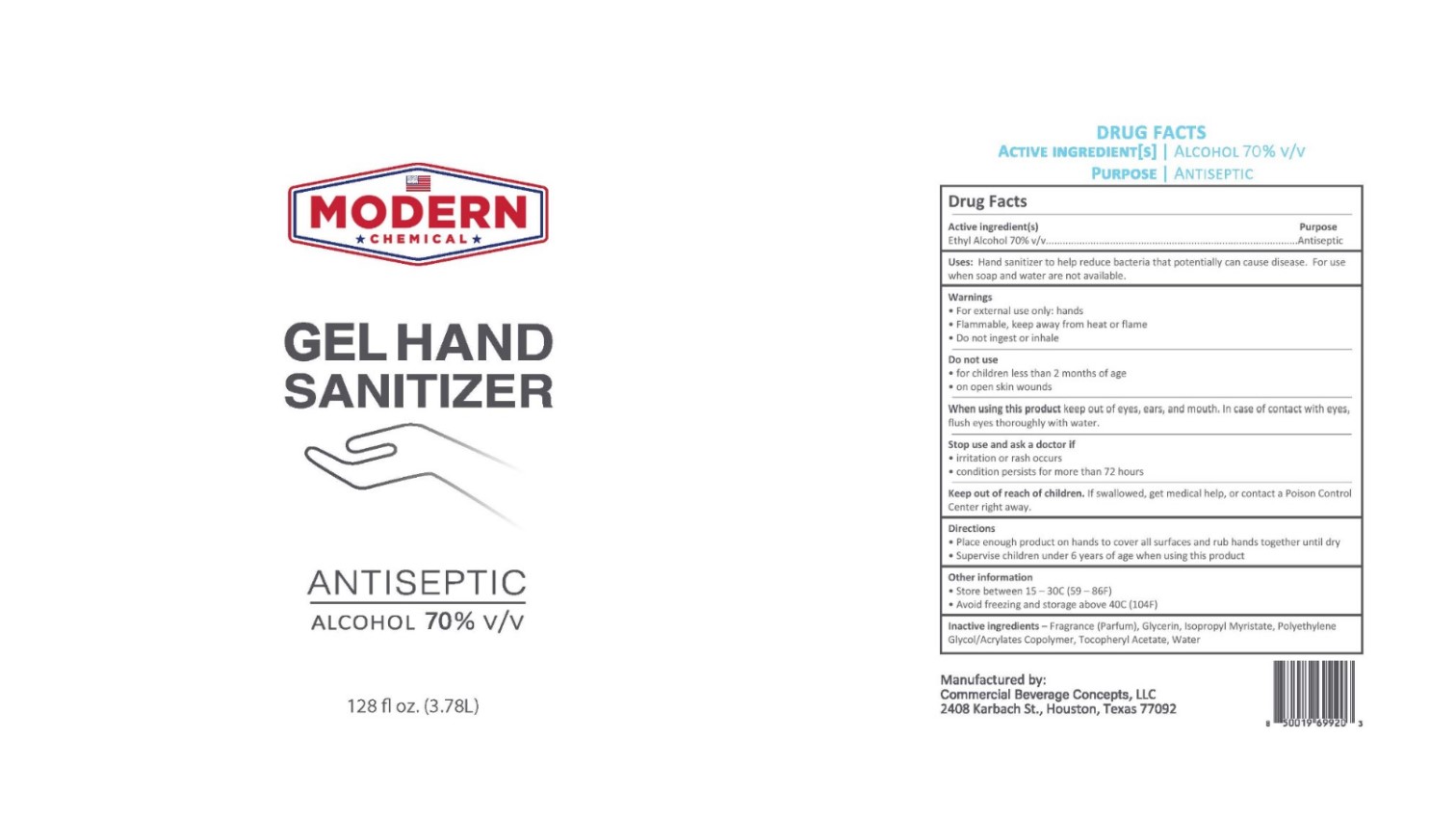 DRUG LABEL: Aloe Gel
NDC: 75594-071 | Form: GEL
Manufacturer: Commercial Beverage Concepts, LLC
Category: otc | Type: HUMAN OTC DRUG LABEL
Date: 20201006

ACTIVE INGREDIENTS: ALCOHOL 0.7 L/1 L
INACTIVE INGREDIENTS: ISOPROPYL MYRISTATE; GLYCERIN; .ALPHA.-TOCOPHEROL ACETATE, DL-; RAPIDGEL EZ1; WATER

Active Ingredient(s)

Alcohol 70% v/v. Purpose: Antiseptic

Purpose

Antiseptic, Hand Sanitizer

Use

Hand Sanitizer to help reduce bacteria that potentially can cause disease. For use when soap and water are not available.

Warnings

For external use only. Flammable. Keep away from heat or flame. Do not ingest or inhale.

Do not use

- in children less than 2 months of age
- on open skin wounds

When using this product keep out of eyes, ears, and mouth. In case of contact with eyes, rinse eyes thoroughly with water.

Stop use and ask a doctor if irritation or rash occurs. These may be signs of a serious condition.

Keep out of reach of children. If swallowed, get medical help or contact a Poison Control Center right away.

Directions

- Place enough product on hands to cover all surfaces. Rub hands together until dry.
- Supervise children under 6 years of age when using this product to avoid swallowing.

Other information

- Store between 15-30C (59-86F)
- Avoid freezing and excessive heat above 40C (104F)

Inactive ingredients

Fragrance (Parfum), Glycerin, Isopropyl Myristate, Polyethylene Glycol/Acrylates Copolymer, Tocopheryl Acetate, Water

PACKAGE LABEL

945.35mL NDC: 75594-071-09

1.89L NDC: 75594-071-10

3.78L NDC: 75594-071-11

237mL NDC: 75594-071-01

354mL NDC:75594-071-03

946mL NDC: 75594-071-04

1.89L NDC: 75594-071-05

3.78L NDC: 75594-071-06

208.198L NDC: 75594-071-07

354mL NDC: 75594-071-16

237mL NDC: 75594-071-17

59ml NDC: 75594-071-18

118ml NDC: 75594-071-19

237ml NDC: 75594-071-20

355ml NDC: 75594-071-21

473ml NDC: 75594-071-22

946ml NDC: 75594-071-23

1.89L NDC: 75594-071-24

3.78L NDC: 75594-071-25